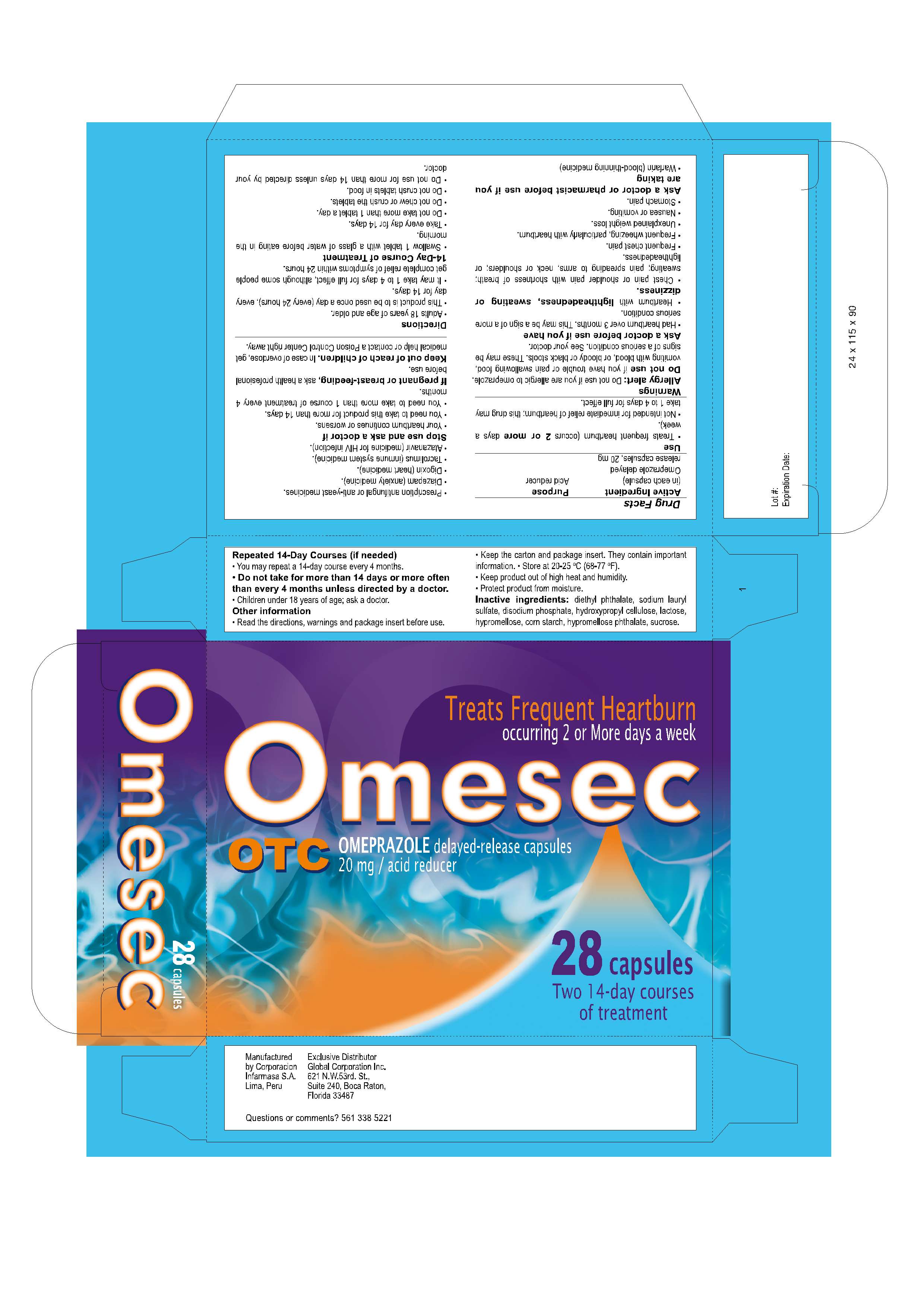 DRUG LABEL: OMESEC
NDC: 16853-1308 | Form: CAPSULE, DELAYED RELEASE
Manufacturer: Corporacion Infarmasa
Category: otc | Type: HUMAN OTC DRUG LABEL
Date: 20100228

ACTIVE INGREDIENTS: OMEPRAZOLE 20 mg/1 1
INACTIVE INGREDIENTS: DIETHYL PHTHALATE 0.144 mg/1 1; SODIUM LAURYL SULFATE 0.432 mg/1 1; SODIUM PHOSPHATE, DIBASIC, DIHYDRATE 0.816 mg/1 1; HYDROXYPROPYL CELLULOSE 6.24 mg/1 1; LACTOSE 8.16 mg/1 1; HYPROMELLOSE 11.81 mg/1 1; STARCH, CORN 24.96 mg/1 1; HYPROMELLOSE PHTHALATE (31% PHTHALATE, 170 CST) 25.18 mg/1 1; SUCROSE 142.26 mg/1 1

Drug Facts

Ask a doctor before use if you have:
* Had heartburn over 3 months. This may be a sign of a more serious condition.
* Heartburn with lightheadedness, sweating or dizziness.
* Chest pain or shoulder pain with shortness of breath, sweating, pain spreading to arms, neck or shoulders, or lightheadedness
* Frequent chest pain.
* Frequent wheezing, particularly with heartburn
* Unexplained weight loss
* Nausea or vomiting
* Stomach pain

Ask a doctor or pharmacist before use if you are taking:

- Warfarin (blood-thinning medicine)
- Prescription antifungal or anti-yeast medicines
- Diazepam (anxiety medicine)
- Digoxin (heart medicine)
- Tacrolimus (immune system medicine)
- Atazanavir (medicine for HIV infection)

Allergy Alert: Do not use if you are allergic to Omeprazole

Do not use if you have trouble or pain swallowing food, vomiting with blood, or bloody or black stools.

These may be signs of a serious condition. See your doctor.

Do not use if capsule blister unit is open or torn

KEEP OUT OF REACH OF CHILDREN

In case of overdose, get medical help or contact a Poison Control Center right away. (1-800-222-1222)

PREGNANCY OR BREAST FEEDING

If pregnant or breast-feeding, ask a health professional before use

Stop use and ask a doctor if an allergic reaction to this product occurs. Seek medical help right away.

Stop use and ask a Doctor if:
* Your heartburn continues or worsens
* You need to take his product for more than 14 days
* You need to take more than 1 course of treatment every 4 months
Do not use if capsule blister unit is open or torn

Use
Treats frequent heartburn (occurs 2 or more days a week)
Not intended for immediate relief of heartburn; this drug may take 1 to 4 days for full effect.

QUESTIONS

If you have questions of a medical nature, please contact your pharmacist, doctor or health care proffesional

STORAGE AND HANDLING

- Read the directions, warnings and package insert before use
- Keep the carton and package insert. They contain important information
- Store at 20ºC to 25ºC (68ºF to 77ºF)
- Keep product out of high heat and humidity
- Protect product from moisture

DOSAGE AND ADMINISTRATION

Adults 18 years of age and older: This product is to be used once a day (every 24 hours), every day for 14 days. It may take 1 to 4 days for full effect, although some people get complete relief of symptoms within 24 hours

14-Day Course of Treatment

- Swallow 1 capsule with a glass of water before eating in the morning
- Take every day for 14 days
- Do not take more than 1 capsule a day
- Do not chew or crush the capsule
- Do not crush capsules in food
- Do not use for more than 14 days unless directed by your doctor

Repeated 14-Day Courses (if needed)

- You may repeat a 14-day course every 4 months
- Do not take more than 14 days or more often than every 4 month unless directed by a doctor

Children under 18 years of age: ask a doctor
Other Information

- Read the directions, warnings and package insert before use

INACTIVE INGREDIENT

Diethyl Phthalate, Sodium Lauryl Sulfate, Disodium Phosphate, Hydroxypropyl Cellulose, Lactose, Hypromellose, Corn Starch, Hypromellose Phthalate, Sucrose

PACKAGE LABEL

Omesec Caps